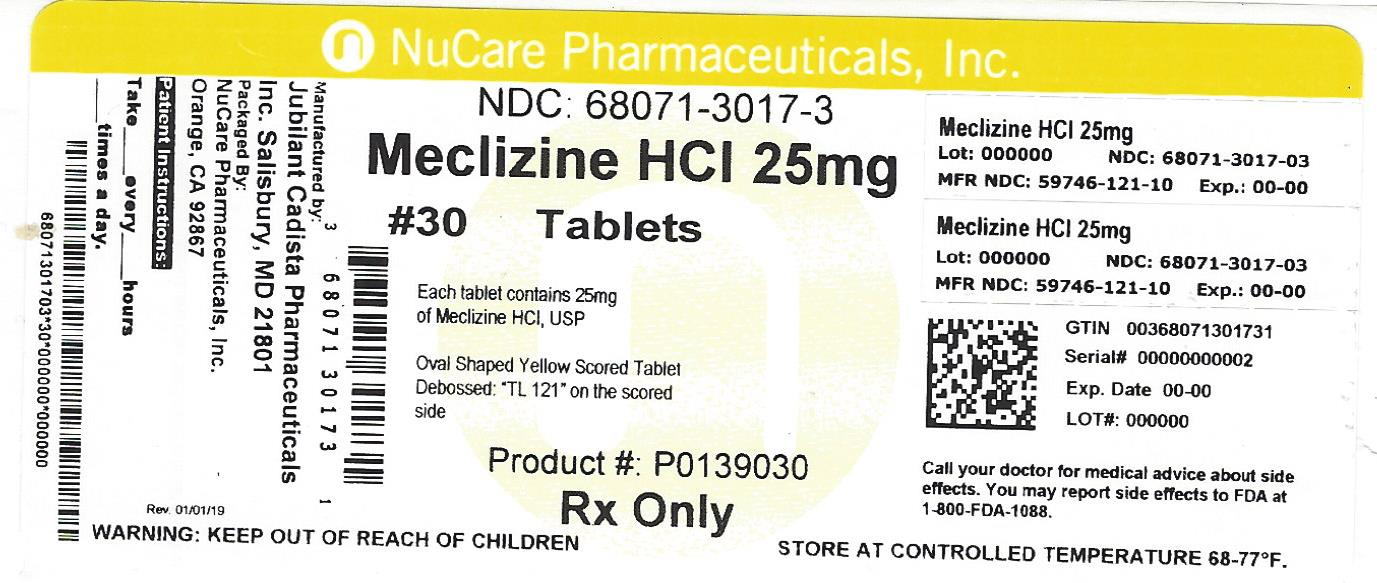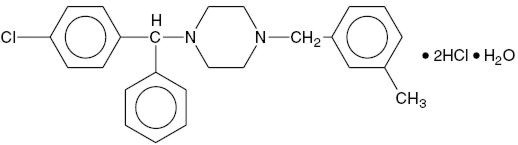 DRUG LABEL: MECLIZINE HYDROCHLORIDE
NDC: 68071-3017 | Form: TABLET
Manufacturer: NuCare Pharmaceuticals,Inc.
Category: prescription | Type: HUMAN PRESCRIPTION DRUG LABEL
Date: 20240717

ACTIVE INGREDIENTS: MECLIZINE HYDROCHLORIDE 25 mg/1 1
INACTIVE INGREDIENTS: SILICON DIOXIDE; CROSCARMELLOSE SODIUM; LACTOSE MONOHYDRATE; MAGNESIUM STEARATE; CELLULOSE, MICROCRYSTALLINE; D&C YELLOW NO. 10; ALUMINUM OXIDE

MECLIZINE HYDROCHLORIDE TABLETS, USP
Rx only

DESCRIPTION

Chemically, Meclizine HCl is 1-(p-chloro-α-phenylbenzyl)-4-(m-methylbenzyl) piperazine dihydrochloride monohydrate.

C25H27ClN2. 2HCl . H2O M .W . 481 .88
Meclizine HCI Tablets, USP are available in two different strengths: 12.5 mg and 25 mg. In addition each tablet contains the following inactive ingredients: Colloidal Silicon Dioxide, Croscarmellose Sodium, Lactose Monohydrate, Magnesium Stearate, Microcrystalline Cellulose. Also, Meclizine HCI Tablets USP, 12.5 mg contains FD&C Blue #1 Aluminum Lake (11-13%) and Meclizine HCI Tablets USP, 25 mg contains D&C Yellow #10 Aluminum Lake (15-20%).

CLINICAL PHARMACOLOGY

Meclizine Hydrochloride is an antihistamine which shows marked protective activity against nebulized histamine and lethal doses of intravenously injected histamine in guinea pigs. It has a marked effect in blocking the vasodepressor response to histamine, but only a slight blocking action against acetylcholine. Its activity is relatively weak in inhibiting the spasmogenic action of histamine on isolated guinea pig ileum.

INDICATIONS AND USAGE

For the management of nausea and vomiting, and dizziness associated with motion sickness.

CONTRAINDICATIONS

Meclizine Hydrochloride is contraindicated in individuals who have shown a previous hypersensitivity to it.

WARNINGS

Since drowsiness may, on occasion, occur with use of this drug, patients should be warned of this possibility and cautioned against driving a car or operating dangerous machinery.
Patients should avoid alcoholic beverages while taking this drug.
Due to its potential anticholinergic action, this drug should be used with caution in patients with asthma, glaucoma or enlargement of the prostate gland.

PRECAUTIONS

PREGNANCY, Teratogenic Effects
Pregnancy Category B. Reproduction studies in rats have shown cleft palates at 25-50 times the human dose. Epidemiological studies in pregnant women, however, do not indicate that medicine increases the risk of abnormalities when administered during pregnancy. Despite the animal findings, it would appear that the possibility of fetal harm is remote. Nevertheless, meclizine, or any other medication, should be used during pregnancy only if clearly necessary.
Pediatric Use
Clinical studies establishing safety and effectiveness in children have not been done; therefore, usage is not recommended in children under 12 years of age.

ADVERSE REACTIONS

Drowsiness, dry mouth and, on rare occasions, blurred vision have been reported.

DOSAGE AND ADMINISTRATION

Motion Sickness
The initial dose of 25 to 50 mg of Meclizine HCI should be taken one hour prior to travel for protection against motion sickness. Thereafter, the dose may be repeated every 24 hours for the duration of the journey.

HOW SUPPLIED

25 mg (Yellow, oval-shaped, scored, debossed with TL121)
NDC 68071-3017-7 BOTTLES OF 10

NDC 68071-3017-1 BOTTLES OF 12

NDC 68071-3017-2 BOTTLES OF 20

NDC 68071-3017-3 BOTTLES OF 30

NDC 68071-3017-6 BOTTLES OF 60

NDC 68071-3017-9 BOTTLES OF 90
Store at 20-25°C (68-77°F) (See USP Controlled Room Temperature].

Manufactured By:
Jubilant Cadista Pharmaceuticals Inc.
Salisbury, MD 21801, USA.

Revised 03/11